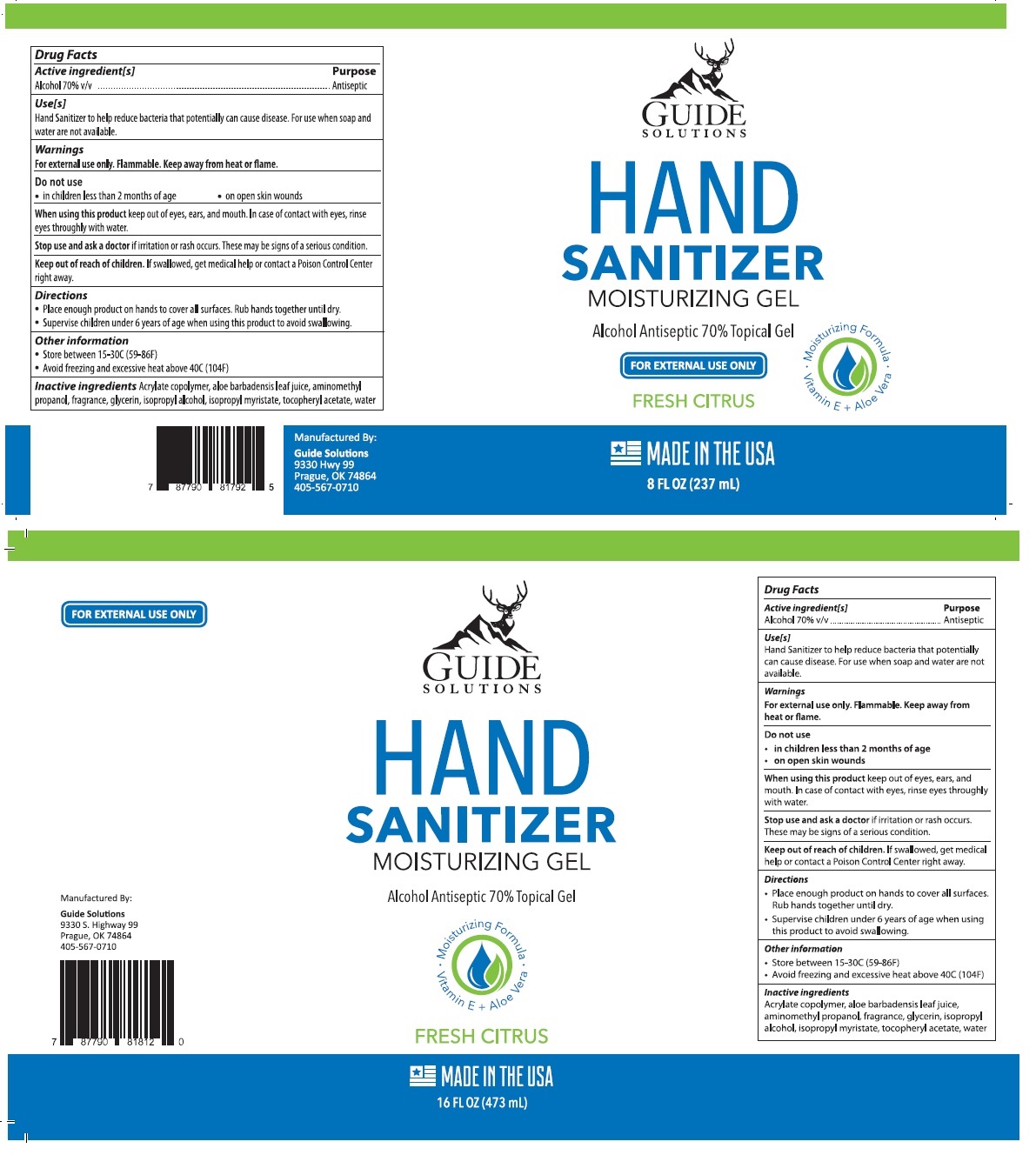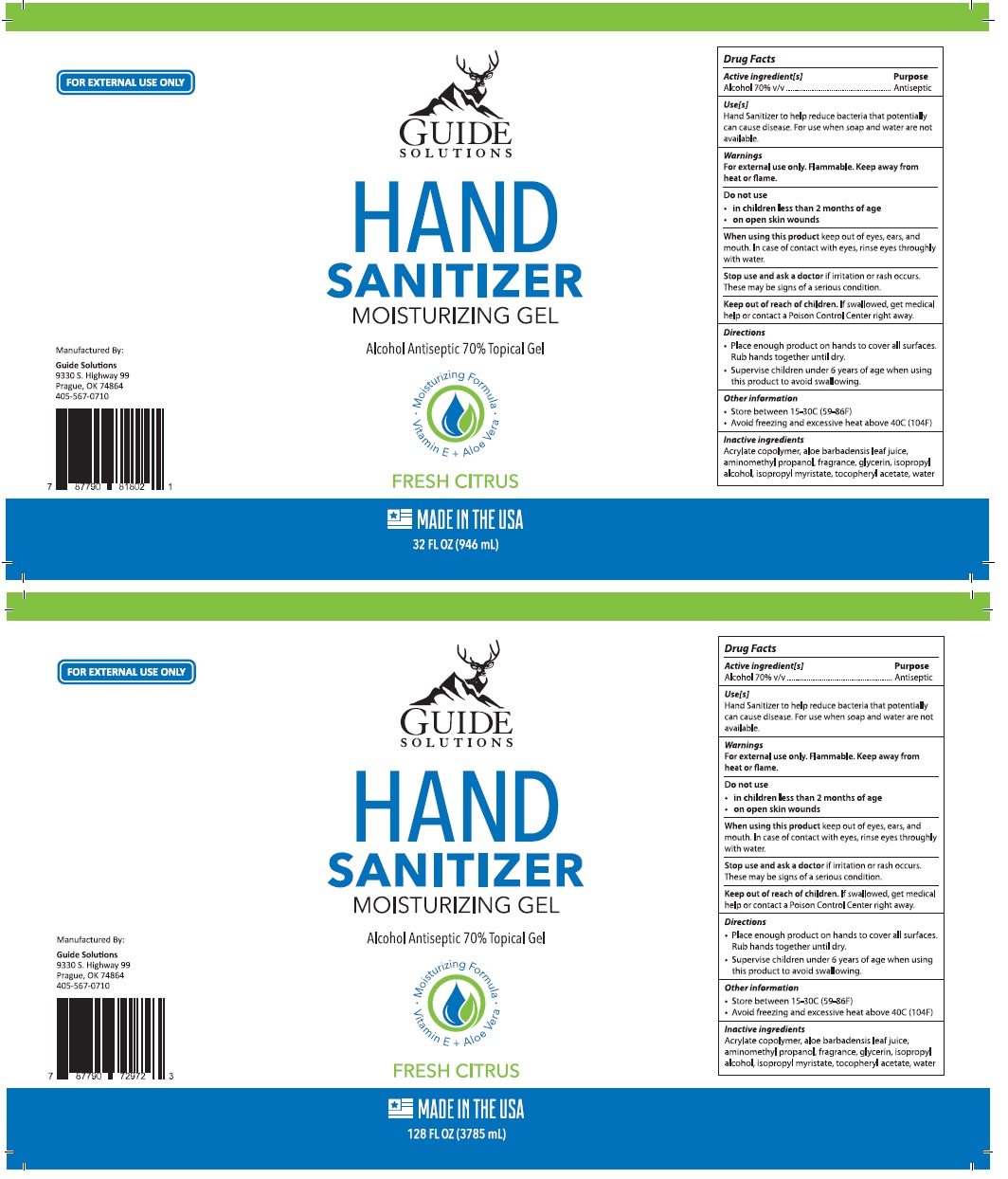 DRUG LABEL: Hand Sanitizer Moisturizing Gel
NDC: 77042-700 | Form: GEL
Manufacturer: Guide Energy Solutions LLC
Category: otc | Type: HUMAN OTC DRUG LABEL
Date: 20211228

ACTIVE INGREDIENTS: ALCOHOL 70 mL/100 mL
INACTIVE INGREDIENTS: METHACRYLIC ACID - ETHYL ACRYLATE COPOLYMER (4500 MPA.S); ALOE VERA LEAF; AMINOMETHYLPROPANOL; GLYCERIN; ISOPROPYL ALCOHOL; ISOPROPYL MYRISTATE; .ALPHA.-TOCOPHEROL ACETATE; WATER

HAND SANITIZER MOISTURIZING GEL

Active ingredient[s]

Alcohol 70% v/v

Purpose

Antiseptic

Uses[s]

Hand Sanitizer to help reduce bacteria that potentially can cause disease. For use when soap and water are not available.

Warnings

For external use only. Flammable. Keep away from heat or flame.

Do not use

- in children less than months of age
- on open skin wounds

When using this product keep out of eyes, ears, and mouth. In case of contact with eyes, rinse eyes thoroughly with water.

Stop use and ask a doctor if irritation or rash occurs. These may be signs of a serious condition.

Keep out of reach of children. If swallowed, get medical help or contact a Poison Control Center right away.

Directions

- Place enough product on hands to cover all surfaces. Rub hands together until dry.
- Supervise children under 6 years of age when using this product to avoid swallowing.

Other information

- Store between 15-30C(59-86F)
- Avoid freezing and excessive heat above 40C(104F)

Inactive ingredients

Acrylates copolymer, aloe barbadensis leaf juice, aminomethyl propanol, fragrance, glycerin, isopropyl alcohol, isopropyl myristate, tocopheryl acetate, water

Alcohol Antiseptic 70% Topical Gel

Moisturizing Formula

Vitamin E + Aloe Vera

FRESH CITRUS

FOR EXTERNAL USE ONLY

MADE IN THE USA

Manufactured By:

Guide Solutions

9330 S. Highway 99

Prague, OK 74864

405-567-0710